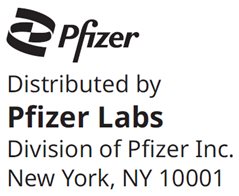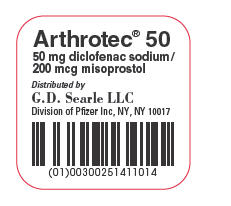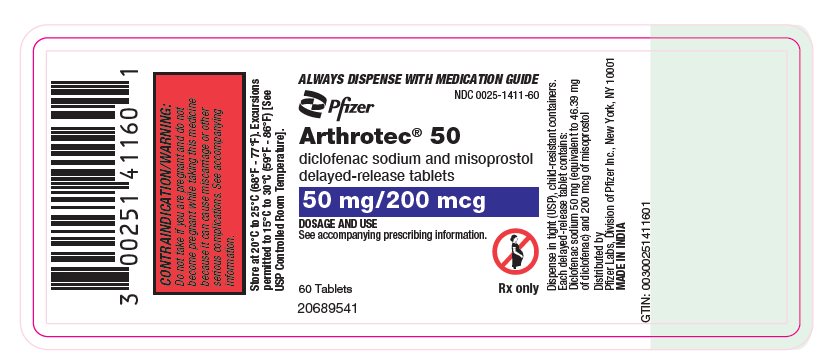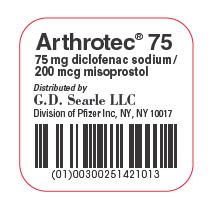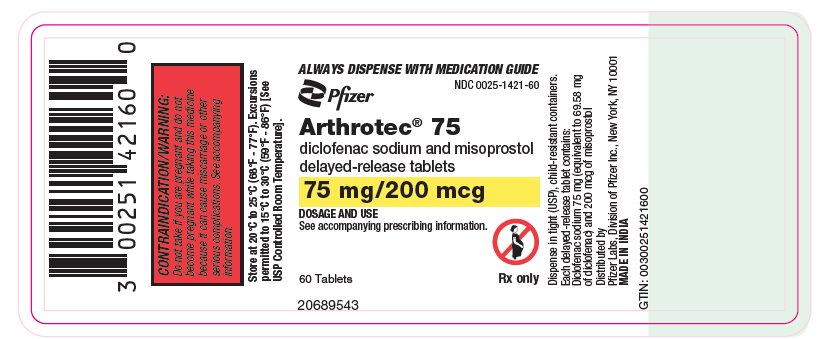 DRUG LABEL: ARTHROTEC
NDC: 0025-1411 | Form: TABLET, FILM COATED
Manufacturer: Pfizer Laboratories Div Pfizer Inc
Category: prescription | Type: HUMAN PRESCRIPTION DRUG LABEL
Date: 20250814

ACTIVE INGREDIENTS: DICLOFENAC SODIUM 50 mg/1 1; MISOPROSTOL 200 ug/1 1
INACTIVE INGREDIENTS: SILICON DIOXIDE; CROSPOVIDONE (120 .MU.M); HYDROGENATED CASTOR OIL; HYPROMELLOSE, UNSPECIFIED; LACTOSE, UNSPECIFIED FORM; MAGNESIUM STEARATE; MICROCRYSTALLINE CELLULOSE; POVIDONE K30; SODIUM HYDROXIDE; STARCH, CORN; TALC; TRIETHYL CITRATE; METHACRYLIC ACID - METHYL METHACRYLATE COPOLYMER (1:1)

HIGHLIGHTS OF PRESCRIBING INFORMATION

These highlights do not include all the information needed to use ARTHROTEC safely and effectively. See full prescribing information for ARTHROTEC.
ARTHROTEC® (diclofenac sodium and misoprostol delayed-release tablets), for oral use
Initial U.S. Approval:1997

RECENT MAJOR CHANGES

Warnings and Precautions, Serious Skin Reactions (5.10) | 11/2024

WARNING: RISK OF UTERINE RUPTURE, ABORTION, PREMATURE BIRTH, BIRTH DEFECTS; SERIOUS CARDIOVASCULAR EVENTS; AND SERIOUS GASTROINTESTINAL EVENTS

See full prescribing information for complete boxed warning.

- Administration of misoprostol, a component of ARTHROTEC, to pregnant women can cause uterine rupture, abortion, premature birth, or birth defects. Uterine rupture has occurred when misoprostol was administered in pregnant women to induce labor or an abortion. (4, 5.1, 8.1)
- ARTHROTEC is contraindicated in pregnancy and is not recommended in women of childbearing potential. Patients must be advised of the abortifacient property and warned not to give the drug to others. (5.1, 8.3)
- Increased risk of serious cardiovascular thrombotic events, including myocardial infarction and stroke, which can be fatal. (5.2)
- ARTHROTEC is contraindicated in the setting of coronary artery bypass graft (CABG) surgery. (4, 5.2)
- Increased risk of serious gastrointestinal (GI) adverse events including bleeding, ulceration, and perforation of the stomach or intestines, which can be fatal and can occur at any time and without warning symptoms. Elderly patients and patients with a prior history of peptic ulcer disease and/or GI bleeding are at greater risk. (5.3)

1 INDICATIONS AND USAGE

ARTHROTEC is a combination of diclofenac sodium, a non-steroidal anti-inflammatory drug, and misoprostol, a prostaglandin-1 (PGE1) analog, indicated for the treatment of signs and symptoms of osteoarthritis or rheumatoid arthritis in adult patients at high risk of developing NSAID-induced gastric and duodenal ulcers and their complications. (1)

2 DOSAGE AND ADMINISTRATION

- Use the lowest effective dosage for the shortest duration consistent with individual patient treatment goals. (2.1)
- Osteoarthritis: The recommended dosage for maximal GI protection is one tablet (containing 50 mg of diclofenac and 200 mcg of misoprostol) three times daily. A dosage of diclofenac higher than 150 mg/day is not recommended. (2.2)
- Rheumatoid Arthritis: The recommended dosage for maximal GI protection is one tablet (containing 50 mg of diclofenac and 200 mcg of misoprostol) three or four times daily A dosage of diclofenac higher than 200 mg/day is not recommended. (2.3)
- For dosage modifications due to intolerance, see the full Prescribing Information. (2.2, 2.3)

3 DOSAGE FORMS AND STRENGTHS

Delayed-release tablets:

- 50 mg diclofenac sodium and 200 mcg misoprostol (3)
- 75 mg diclofenac sodium and 200 mcg misoprostol (3)

4 CONTRAINDICATIONS

- Pregnancy (4)
- In the setting of CABG surgery (4)
- Active gastrointestinal bleeding (4)
- History of asthma, urticaria, or other allergic-type reactions after taking aspirin or other NSAIDs (4)
- Known hypersensitivity to diclofenac sodium, misoprostol, or any components of the drug product (4)

5 WARNINGS AND PRECAUTIONS

- Embryo-Fetal Toxicity with NSAIDs: Use of NSAIDs, including diclofenac in women at about 20 weeks gestation and later in pregnancy may cause oligohydramnios/fetal renal dysfunction and premature closure of the fetal ductus arteriosus. (4, 5.1, 8.1)
- Hepatotoxicity: Inform patients of warning signs and symptoms of hepatotoxicity. Discontinue if abnormal liver tests persist or worsen or if clinical signs and symptoms of liver disease develop. (5.4)
- Hypertension: Patients taking some antihypertensive medications may have impaired response to these therapies when taking NSAIDs. Monitor blood pressure. (5.5, 7)
- Heart Failure and Edema: Avoid in patients with severe heart failure unless benefits are expected to outweigh risk of worsening heart failure. (5.6)
- Renal Toxicity: Monitor renal function in patients with renal or hepatic impairment, heart failure, dehydration, or hypovolemia. Avoid in patients with advanced renal disease unless benefits are expected to outweigh risk of worsening renal function. (5.7)
- Anaphylactic Reactions: Seek emergency help if an anaphylactic reaction occurs. (5.8)
- Exacerbation of Asthma Related to Aspirin Sensitivity: Contraindicated in patients with aspirin-sensitive asthma. Monitor patients with preexisting asthma (without aspirin sensitivity). (5.9)
- Serious Skin Reactions: Discontinue at first appearance of skin rash or other signs of hypersensitivity. (5.10)
- Drug Reaction with Eosinophilia and Systemic Symptoms (DRESS): Discontinue and evaluate clinically. (5.11)
- Hematologic Toxicity: Monitor hemoglobin or hematocrit in patients with any signs or symptoms of anemia. (5.12, 7)

6 ADVERSE REACTIONS

Most common adverse reactions (>2%) are: abdominal pain, diarrhea, dyspepsia, nausea, flatulence, gastritis, vomiting, constipation, headache, dizziness, alanine aminotransferase increased, hematocrit decreased (6.1)

To report SUSPECTED ADVERSE REACTIONS, contact Pfizer Inc.at 1-800-438-1985 or FDA at 1-800-FDA-1088 or www.fda.gov/medwatch.

7 DRUG INTERACTIONS

See full prescribing information for a list of clinically important drug interactions. (7)

8 USE IN SPECIFIC POPULATIONS

- Reversible Infertility: Consider withdrawal in women who have difficulties conceiving. (8.3)
- Geriatric Patients: Avoid use in patients with cardiovascular and/or renal risk factors. (8.5)
- Renal Impairment: Avoid use in patients with advanced renal disease. (8.6)

FULL PRESCRIBING INFORMATION

WARNING: RISK OF UTERINE RUPTURE, ABORTION, PREMATURE BIRTH, BIRTH DEFECTS; SERIOUS CARDIOVASCULAR EVENTS; AND SERIOUS GASTROINTESTINAL EVENTS

Uterine Rupture, Abortion, Premature Birth, and Birth Defects

- Administration of misoprostol, a component of ARTHROTEC, to pregnant women can cause uterine rupture, abortion, premature birth, or birth defects. Uterine rupture has occurred when misoprostol was administered in pregnant women to induce labor or an abortion [see Warnings and Precautions (5.1) and Use in Specific Populations (8.1)].
- ARTHROTEC is contraindicated in pregnancy [see Contraindications (4)] and not recommended in women of childbearing potential. Patients must be advised of the abortifacient property and warned not to give the drug to others [see Warnings and Precautions (5.1)].
- If ARTHROTEC is prescribed, verify the pregnancy status of females of reproductive potential prior to initiation of treatment and advise them to use effective contraception during treatment [see Use in Specific Populations (8.3)].

Cardiovascular Thrombotic Events

- NSAIDs cause an increased risk of serious cardiovascular thrombotic events, including myocardial infarction and stroke, which can be fatal. This risk may occur early in treatment and may increase with duration of use [see Warnings and Precautions (5.2)].
- ARTHROTEC is contraindicated in the setting of coronary artery bypass graft (CABG) surgery [see Contraindications (4) and Warnings and Precautions (5.2)].

Gastrointestinal Bleeding, Ulceration, and Perforation

- NSAIDs cause an increased risk of serious gastrointestinal (GI) adverse events including bleeding, ulceration, and perforation of the stomach or intestines, which can be fatal. These events can occur at any time during use and without warning symptoms. Elderly patients and patients with a prior history of peptic ulcer disease and/or GI bleeding are at greater risk for serious GI events [see Warnings and Precautions (5.3)].

1 INDICATIONS AND USAGE

ARTHROTEC is indicated for treatment of the signs and symptoms of osteoarthritis or rheumatoid arthritis in adult patients at high risk of developing NSAID-induced gastric and duodenal ulcers and their complications. For a list of factors that may increase the risk of NSAID-induced gastric and duodenal ulcers and their complications [see Warnings and Precautions (5.3)].

2 DOSAGE AND ADMINISTRATION

2.1 Important Dosage Information

- Carefully consider the potential benefits and risks of ARTHROTEC and other treatment options before deciding to use ARTHROTEC. Use the lowest effective dosage for the shortest duration consistent with individual patient treatment goals [see Warnings and Precautions (5)].
- After observing the response to initial therapy with ARTHROTEC, the dose and frequency should be adjusted to suit an individual patient's needs.
- ARTHORTEC is not recommended for patients who would not receive the appropriate dosage of both active ingredients.
- ARTHROTEC, a fixed combination product, is administered as
  ARTHROTEC 50 (50 mg diclofenac sodium and 200 mcg misoprostol) or
  ARTHROTEC 75 (75 mg diclofenac sodium and 200 mcg misoprostol).

2.2 Recommended Dosage in Patients with Osteoarthritis

The recommended dosage for the treatment of osteoarthritis for maximal GI mucosal protection is ARTHROTEC 50 three times a day. For patients who experience intolerance, ARTHROTEC 75 two times a day or ARTHROTEC 50 two times a day can be used, but these dosages are less effective in preventing ulcers. A daily dosage of diclofenac sodium greater than 150 mg/day is not recommended. Daily doses of the components delivered with these regimens are as follows:

 | Osteoarthritis Regimen | Diclofenac sodium (mg/day) | Misoprostol (mcg/day)
ARTHROTEC 50 | three times a day | 150 | 600
 | two times a day [For patients who experience intolerance; these dosages are less effective in preventing ulcers] | 100 | 400
ARTHROTEC 75 | two times a day | 150 | 400

2.3 Recommended Dosage in Patients with Rheumatoid Arthritis

The recommended dosage for the treatment of rheumatoid arthritis is ARTHROTEC 50 three or four times a day. For patients who experience intolerance, ARTHROTEC 75 two times a day or ARTHROTEC 50 two times a day can be used, but are less effective in preventing ulcers. A daily dosage of diclofenac sodium greater than 200 mg/day is not recommended. Daily doses of the components delivered with these regimens are as follows:

 | Rheumatoid Arthritis Regimen | Diclofenac sodium (mg/day) | Misoprostol (mcg/day)
ARTHROTEC 50 | four times a day | 200 | 800
 | three times a day | 150 | 600
 | two times a day [For patients who experience intolerance; these dosages are less effective in preventing ulcers] | 100 | 400
ARTHROTEC 75 | two times a day | 150 | 400

2.4 Additional Dosage Recommendations

ARTHROTEC contains misoprostol, which provides protection against gastric and duodenal ulcers [see Clinical Studies (14)]. For gastric ulcer prevention, the 200 mcg four and three times a day regimens are therapeutically equivalent, but more protective than the two times a day regimen. For duodenal ulcer prevention, the four times a day regimen is more protective than the three or two times a day regimens. However, the four times a day regimen is less well tolerated than the three times a day regimen because of usually self-limited diarrhea related to the misoprostol dose [see Adverse Reactions (6.1)], and the two times a day regimen may be better tolerated than three times a day in some patients.

Dosages may be individualized using the separate products (misoprostol and diclofenac sodium), after which the patient may be switched to the appropriate ARTHROTEC dosage. If clinically indicated, misoprostol co-therapy with ARTHROTEC to optimize the misoprostol dose and/or frequency of administration, may be appropriate. Do not exceed a total misoprostol dose of 800 mcg/day and do not administer more than 200 mcg of misoprostol at any one time.

When concomitant use of CYP2C9 inhibitors is necessary, the maximum total daily dose of diclofenac is 100 mg per day. Do not exceed a dosage of ARTHOTEC 50 mg twice daily [see Drug Interactions (7)].

For additional information, refer to the Prescribing Information for the individual products of diclofenac sodium and misoprostol.

3 DOSAGE FORMS AND STRENGTHS

Delayed-release tablets:

- 50 mg diclofenac sodium and 200 mcg misoprostol as round, biconvex, white to off-white tablets imprinted with four "A's" encircling a "50" in the middle on one side and "SEARLE" and "1411" on the other.
- 75 mg diclofenac sodium and 200 mcg misoprostol as round, biconvex, white to off-white tablets imprinted with four "A's" encircling a "75" in the middle on one side and "SEARLE" and "1421" on the other.

4 CONTRAINDICATIONS

ARTHROTEC is contraindicated in the following patients:

- Pregnancy. Use of misoprostol, a component of ARTHROTEC, during pregnancy can result in maternal and fetal harm, including uterine rupture, abortion, premature birth, or birth defects [see Warnings and Precautions (5.1) and Use in Specific Populations (8.1)]
- In the setting of coronary artery bypass graft (CABG) surgery [see Warnings and Precautions (5.2)]
- Active gastrointestinal bleeding [see Warnings and Precautions (5.3)]
- History of asthma, urticaria, or other allergic-type reactions after taking aspirin or other NSAIDs. Severe, sometimes fatal, anaphylactic reactions to NSAIDs have been reported in such patients [see Warnings and Precautions (5.8, 5.9)]
- Known hypersensitivity (e.g., anaphylactic reactions and serious skin reactions) to diclofenac sodium and misoprostol, other prostaglandins, or any components of the drug product [see Warnings and Precautions (5.8, 5.10)]

5 WARNINGS AND PRECAUTIONS

5.1 Uterine Rupture, Abortion, Premature Birth, or Birth Defects with Misoprostol and Embryo-Fetal Toxicity with NSAIDs

Misoprostol

Administration of misoprostol, a component of ARTHROTEC, to pregnant women can cause uterine rupture, abortion, premature birth, or birth defects. Uterine rupture has occurred when misoprostol was administered to pregnant women to induce labor or an abortion.

ARTHROTEC is contraindicated in pregnant women. ARTHROTEC is not recommended in women of childbearing potential. Patients must be advised of the abortifacient property and warned not to give the drug to others [see Use in Specific Populations (8.1)].

If ARTHROTEC is prescribed, verify the pregnancy status of females of reproductive potential prior to initiation of treatment and advise the use effective contraception during treatment with ARTHROTEC [see Use in Specific Populations (8.3)].

Diclofenac

Premature Closure of Fetal Ductus Arteriosus

NSAIDs, including diclofenac, a component of ARTHROTEC, increase the risk of premature closure of the fetal ductus arteriosus at about 30 weeks of gestation and later.

Oligohydramnios/Neonatal Renal Impairment

Use of NSAIDs, including diclofenac, at about 20 weeks gestation or later in pregnancy may cause fetal renal dysfunction leading to oligohydramnios and, in some cases, neonatal renal impairment. These adverse outcomes are seen, on average, after days to weeks of treatment, although oligohydramnios has been infrequently reported as soon as 48 hours after NSAID initiation. Oligohydramnios is often, but not always, reversible with treatment discontinuation. Complications of prolonged oligohydramnios may, for example, include limb contractures and delayed lung maturation. In some postmarketing cases of impaired neonatal renal function, invasive procedures such as exchange transfusion or dialysis were required [see Use in Specific Populations (8.1)].

5.2 Cardiovascular Thrombotic Events

Clinical trials of several cyclooxygenase-2 (COX-2) selective and nonselective NSAIDs of up to three years duration have shown an increased risk of serious cardiovascular (CV) thrombotic events, including myocardial infarction (MI) and stroke, which can be fatal. Based on available data, it is unclear that the risk for CV thrombotic events is similar for all NSAIDs. The relative increase in serious CV thrombotic events over baseline conferred by NSAID use appears to be similar in those with and without known CV disease or risk factors for CV disease. However, patients with known CV disease or risk factors had a higher absolute incidence of excess serious CV thrombotic events, due to their increased baseline rate. Some observational studies found that this increased risk of serious CV thrombotic events began as early as the first weeks of treatment. The increase in CV thrombotic risk has been observed most consistently at higher doses.

To minimize the potential risk for an adverse CV event in NSAID-treated patients, use the lowest effective dose for the shortest duration possible. Physicians and patients should remain alert for the development of such events, throughout the entire treatment course, even in the absence of previous CV symptoms. Patients should be informed about the symptoms of serious CV events and the steps to take if they occur.

There is no consistent evidence that concurrent use of aspirin mitigates the increased risk of serious CV thrombotic events associated with NSAID use. The concurrent use of aspirin and an NSAID, such as diclofenac, increases the risk of serious gastrointestinal (GI) events [see Warnings and Precautions (5.3)].

Status Post Coronary Artery Bypass Graft (CABG) Surgery

Two large, controlled clinical trials of a COX-2 selective NSAID for the treatment of pain in the first 10 to 14 days following CABG surgery found an increased incidence of myocardial infarction and stroke. NSAIDs are contraindicated in the setting of CABG [see Contraindications (4)].

Post-MI Patients

Observational studies conducted in the Danish National Registry have demonstrated that patients treated with NSAIDs in the post-MI period were at increased risk of reinfarction, CV-related death, and all-cause mortality beginning in the first week of treatment. In this same cohort, the incidence of death in the first year post-MI was 20 per 100 person years in NSAID-treated patients compared to 12 per 100 person years in non-NSAID exposed patients. Although the absolute rate of death declined somewhat after the first year post-MI, the increased relative risk of death in NSAID users persisted over at least the next four years of follow-up.

Avoid the use of ARTHROTEC in patients with a recent MI unless the benefits are expected to outweigh the risk of recurrent CV thrombotic events. If ARTHROTEC is used in patients with a recent MI, monitor patients for signs of cardiac ischemia.

5.3 Gastrointestinal Bleeding, Ulceration, and Perforation

NSAIDs, including diclofenac, cause serious gastrointestinal (GI) adverse events including inflammation, bleeding, ulceration, and perforation of the esophagus, stomach, small intestine, or large intestine, which can be fatal. These serious adverse events can occur at any time, with or without warning symptoms, in patients treated with NSAIDs. Only one in five patients who develop a serious upper GI adverse event on NSAID therapy is symptomatic. Upper GI ulcers, gross bleeding, or perforation caused by NSAIDs occurred in approximately 1% of patients treated for 3 to 6 months, and in about 2% to 4% of patients treated for one year. However, even short-term NSAID therapy is not without risk.

Risk Factors for GI Bleeding, Ulceration, and Perforation

Patients with a prior history of peptic ulcer disease and/or GI bleeding who used NSAIDs had a greater than 10-fold increased risk for developing a GI bleed compared to patients without these risk factors. Other factors that increase the risk of GI bleeding in patients treated with NSAIDs include longer duration of NSAID therapy; concomitant use of oral corticosteroids, antiplatelet drugs (such as aspirin), anticoagulants, or selective serotonin reuptake inhibitors (SSRIs); smoking; use of alcohol; older age; and poor general health status. Most postmarketing reports of fatal GI events occurred in elderly or debilitated patients. Additionally, patients with advanced liver disease and/or coagulopathy are at increased risk for GI bleeding.

Strategies to Minimize the GI Risks in NSAID-treated patients:

- Use the lowest effective dosage for the shortest possible duration.
- Avoid administration of more than one NSAID at a time.
- Remain alert for signs and symptoms of GI ulceration and bleeding during NSAID therapy.
- If a serious GI adverse event is suspected, promptly initiate evaluation and treatment, and discontinue ARTHROTEC until a serious GI adverse event is ruled out.
- In the setting of concomitant use of low-dose aspirin for cardiac prophylaxis, monitor patients more closely for evidence of GI bleeding [see Drug Interactions (7)].

5.4 Hepatotoxicity

In clinical trials with ARTHROTEC, meaningful elevation of alanine aminotransferase (ALT) (serum glutamic pyruvic transaminase [SGPT], more than 3 times the upper limit of the normal range [ULN]) occurred in 1.6% of 2,184 patients treated with ARTHROTEC and in 1.4% of 1,691 patients treated with diclofenac sodium. These increases were generally transient, and enzyme levels returned to within the normal range upon discontinuation of therapy with ARTHROTEC. The misoprostol component of ARTHROTEC does not appear to exacerbate the hepatic effects caused by the diclofenac sodium component.

In clinical trials of diclofenac-containing products, meaningful elevations (i.e., more than 3 times the ULN) of aspartate aminotransferase (AST) (serum glutamic-oxaloacetic transaminase [SGOT]) occurred in about 2% of approximately 5,700 patients at some time during diclofenac treatment (ALT was not measured in all studies).

In a large, open-label, controlled trial of 3,700 patients treated with oral diclofenac sodium for 2 to 6 months, patients were monitored first at 8 weeks and 1,200 patients were monitored again at 24 weeks. Meaningful elevations of ALT and/or AST occurred in about 4% of patients and included marked elevations (i.e., greater than 8 times the ULN) in about 1% of the 3,700 patients. In that open-label study, a higher incidence of borderline (less than 3 times the ULN), moderate (3 to 8 times the ULN), and marked (greater than 8 times the ULN) elevations of ALT or AST was observed in patients receiving diclofenac when compared to other NSAIDs. Elevations in transaminases were seen more frequently in patients with osteoarthritis than in those with rheumatoid arthritis.

Almost all meaningful elevations in transaminases were detected before patients became symptomatic. Abnormal tests occurred during the first 2 months of therapy with diclofenac in 42 of the 51 patients in all trials who developed marked transaminase elevations.

In postmarketing reports, cases of drug-induced hepatotoxicity have been reported in the first month, and in some cases, the first 2 months of therapy, but can occur at any time during treatment with diclofenac. Postmarketing surveillance has reported cases of severe hepatic reactions, including liver necrosis, jaundice, fulminant hepatitis with and without jaundice, and liver failure. Some of these reported cases resulted in fatalities or liver transplantation.

In a European retrospective population-based, case-controlled study, 10 cases of diclofenac associated drug-induced liver injury with current use compared with non-use of diclofenac were associated with a statistically significant 4-fold adjusted odds ratio of liver injury. In this particular study, based on an overall number of 10 cases of liver injury associated with diclofenac, the adjusted odds ratio increased further with female gender, doses of 150 mg or more, and duration of use for more than 90 days.

Physicians should measure transaminases at baseline and periodically in patients receiving long-term therapy with diclofenac, because severe hepatotoxicity may develop without a prodrome of distinguishing symptoms. The optimum times for making the first and subsequent transaminase measurements are not known. Based on clinical trial data and postmarketing experiences, transaminases should be monitored within 4 to 8 weeks after initiating treatment with diclofenac. However, severe hepatic reactions can occur at any time during treatment with diclofenac.

If abnormal liver tests persist or worsen, if clinical signs and/or symptoms consistent with liver disease develop, or if systemic manifestations occur (e.g., eosinophilia, rash, abdominal pain, diarrhea, dark urine, etc.), ARTHROTEC should be discontinued immediately.

Inform patients of the warning signs and symptoms of hepatotoxicity (e.g., nausea, fatigue, lethargy, diarrhea, pruritus, jaundice, right upper quadrant tenderness, and "flu-like" symptoms). If clinical signs and symptoms consistent with liver disease develop, or if systemic manifestations occur (e.g., eosinophilia, rash, etc.), discontinue ARTHROTEC immediately, and perform a clinical evaluation of the patient.

To minimize the potential risk for an adverse liver related event in patients treated with ARTHROTEC, the lowest effective dose should be used for the shortest duration possible. Exercise caution when prescribing ARTHROTEC with concomitant drugs that are known to be potentially hepatotoxic (e.g., antibiotics, anti-epileptics).

5.5 Hypertension

NSAIDs, including diclofenac, a component of ARTHROTEC, can lead to new onset of hypertension or worsening of pre-existing hypertension, either of which may contribute to the increased incidence of CV events. Patients taking angiotensin converting enzyme (ACE) inhibitors, thiazide diuretics, or loop diuretics may have impaired response to these therapies when taking NSAIDs [see Drug Interactions (7)].

Monitor blood pressure (BP) during the initiation of NSAID treatment and throughout the course of therapy.

5.6 Heart Failure and Edema

The Coxib and traditional NSAID Trialists' Collaboration meta-analysis of randomized controlled trials demonstrated an approximately two-fold increase in hospitalizations for heart failure in COX-2 selective-treated patients and nonselective NSAID-treated patients compared to placebo-treated patients. In a Danish National Registry study of patients with heart failure, NSAID use increased the risk of MI, hospitalization for heart failure, and death.

Additionally, fluid retention and edema have been observed in some patients treated with NSAIDs. Use of diclofenac may blunt the CV effects of several therapeutic agents used to treat these medical conditions (e.g., diuretics, ACE inhibitors, or angiotensin receptor blockers [ARBs]) [see Drug Interactions (7)].

Avoid the use of ARTHROTEC in patients with severe heart failure unless the benefits are expected to outweigh the risk of worsening heart failure. If ARTHROTEC is used in patients with severe heart failure, monitor patients for signs of worsening heart failure.

5.7 Renal Toxicity and Hyperkalemia

Renal Toxicity

Long-term administration of NSAIDs has resulted in renal papillary necrosis and other renal injury. Renal toxicity has also been seen in patients in whom renal prostaglandins have a compensatory role in the maintenance of renal perfusion. In these patients, administration of an NSAID may cause a dose-dependent reduction in prostaglandin formation and, secondarily, in renal blood flow, which may precipitate overt renal decompensation. Patients at greatest risk of this reaction are those with impaired renal function, dehydration, hypovolemia, heart failure, liver dysfunction, those taking diuretics and ACE inhibitors or ARBs, and the elderly. Discontinuation of NSAID therapy is usually followed by recovery to the pretreatment state.

No information is available from controlled clinical studies regarding the use of ARTHROTEC in patients with advanced renal disease. The renal effects of ARTHROTEC may hasten the progression of renal dysfunction in patients with pre-existing renal disease.

Correct volume status in dehydrated or hypovolemic patients prior to initiating ARTHROTEC. Monitor renal function in patients with renal or hepatic impairment, heart failure, dehydration, or hypovolemia during use of ARTHROTEC [see Drug Interactions (7)]. Avoid the use of ARTHROTEC in patients with advanced renal disease unless the benefits are expected to outweigh the risk of worsening renal function. If ARTHROTEC is used in patients with advanced renal disease, monitor patients for signs of worsening renal function.

Hyperkalemia

Increases in serum potassium concentration, including hyperkalemia, with use of NSAIDs, even in some patients without renal impairment. In patients with normal renal function, these effects have been attributed to a hyporeninemic-hypoaldosteronism state.

5.8 Anaphylactic Reactions

ARTHROTEC has been associated with anaphylactic reactions in patients with and without known hypersensitivity to the individual components of diclofenac sodium and misoprostol and in patients with aspirin-sensitive asthma [see Contraindications (4) and Warnings and Precautions (5.9)].

Seek emergency help if an anaphylactic reaction occurs.

5.9 Exacerbation of Asthma Related to Aspirin Sensitivity

A subpopulation of patients with asthma may have aspirin-sensitive asthma which may include chronic rhinosinusitis complicated by nasal polyps; severe, potentially fatal bronchospasm; and/or intolerance to aspirin and other NSAIDs. Because cross-reactivity between aspirin and other NSAIDs has been reported in such aspirin-sensitive patients, ARTHROTEC is contraindicated in patients with this form of aspirin sensitivity [see Contraindications (4)]. When ARTHROTEC is used in patients with preexisting asthma (without known aspirin sensitivity), monitor patients for changes in the signs and symptoms of asthma.

5.10 Serious Skin Reactions

NSAIDs, including diclofenac, a component of ARTHROTEC, can cause serious skin adverse reactions such as exfoliative dermatitis, Stevens-Johnson Syndrome (SJS), and toxic epidermal necrolysis (TEN), which can be fatal. NSAIDs can also cause fixed drug eruption (FDE). FDE may present as a more severe variant known as generalized bullous fixed drug eruption (GBFDE), which can be life-threatening. These serious events may occur without warning. Inform patients about the signs and symptoms of serious skin reactions, and to discontinue the use of ARTHROTEC at the first appearance of skin rash or any other sign of hypersensitivity. ARTHROTEC is contraindicated in patients with previous serious skin reactions to NSAIDs [see Contraindications (4)].

5.11 Drug Reaction with Eosinophilia and Systemic Symptoms (DRESS)

Drug Reaction with Eosinophilia and Systemic Symptoms (DRESS) has been reported in patients taking NSAIDs such as ARTHROTEC. Some of these events have been fatal or life-threatening. DRESS typically, although not exclusively, presents with fever, rash, lymphadenopathy, and/or facial swelling. Other clinical manifestations may include hepatitis, nephritis, hematological abnormalities, myocarditis, or myositis. Sometimes symptoms of DRESS may resemble an acute viral infection. Eosinophilia is often present. Because this disorder is variable in its presentation, other organ systems not noted here may be involved. It is important to note that early manifestations of hypersensitivity, such as fever or lymphadenopathy, may be present even though rash is not evident. If such signs or symptoms are present, discontinue ARTHROTEC and evaluate the patient immediately.

5.12 Hematologic Toxicity

Anemia has occurred in NSAID-treated patients. This may be due to occult or gross blood loss, fluid retention, or an incompletely described effect on erythropoiesis. If a patient treated with ARTHROTEC has any signs or symptoms of anemia, monitor hemoglobin or hematocrit.

NSAIDs, including diclofenac a component ARTHROTEC, may increase the risk of bleeding events. Co-morbid conditions such as coagulation disorders or concomitant use of warfarin and other anticoagulants, antiplatelet drugs (e.g., aspirin), and SSRIs and serotonin norepinephrine reuptake inhibitors (SNRIs) may increase this risk. Monitor these patients for signs of bleeding [see Drug Interactions (7)].

5.13 Masking of Inflammation and Fever

The pharmacological activity of diclofenac, a component of ARTHROTEC, in reducing inflammation, and possibly fever, may diminish the utility of diagnostic signs in detecting infections.

5.14 Laboratory Monitoring

Because serious GI bleeding, hepatotoxicity, and renal injury can occur without warning symptoms or signs, consider monitoring patients on long-term NSAID treatment with a complete blood count (CBC) and a chemistry profile periodically [see Warnings and Precautions (5.3, 5.7)].

6 ADVERSE REACTIONS

The following adverse reactions are discussed in greater detail in other sections of the labeling:

- Cardiovascular Thrombotic Events [see Warnings and Precautions (5.2)]
- GI Bleeding, Ulceration and Perforation [see Warnings and Precautions (5.3)]
- Hepatotoxicity [see Warnings and Precautions (5.4)]
- Hypertension [see Warnings and Precautions (5.5)]
- Heart Failure and Edema [see Warnings and Precautions (5.6)]
- Renal Toxicity and Hyperkalemia [see Warnings and Precautions (5.7)]
- Anaphylactic Reactions [see Warnings and Precautions (5.8)]
- Serious Skin Reactions [see Warnings and Precautions (5.10)]
- Hematologic Toxicity [see Warnings and Precautions (5.12)]

6.1 Clinical Trials Experience

Because clinical trials are conducted under widely varying conditions, adverse reaction rates observed in the clinical trials of a drug cannot be directly compared to rates in the clinical trials of another drug and may not reflect the rates observed in practice.

Adverse reaction information for ARTHROTEC is derived from multinational controlled clinical trials in over 2,000 patients receiving ARTHROTEC 50 or ARTHROTEC 75, as well as from blinded, controlled trials of diclofenac sodium delayed-release tablets and misoprostol tablets.

Gastrointestinal

GI disorders had the highest reported incidence of adverse reactions for patients receiving ARTHROTEC. These events were generally minor, but led to discontinuation of therapy in 9% of patients on ARTHROTEC and 5% of patients on diclofenac sodium. For GI ulcer rates, [see Clinical Studies (14)].

GI disorder | ARTHROTEC | Diclofenac Sodium
Abdominal pain | 21% | 15%
Diarrhea | 19% | 11%
Dyspepsia | 14% | 11%
Nausea | 11% | 6%
Flatulence | 9% | 4%

ARTHROTEC can cause more abdominal pain, diarrhea, and other GI symptoms than diclofenac alone.

Diarrhea and abdominal pain developed early in the course of therapy, and were usually self-limited (resolved after 2 to 7 days). Rare instances of profound diarrhea leading to severe dehydration have been reported in patients receiving misoprostol. Patients with an underlying condition such as inflammatory bowel disease, or those in whom dehydration, were it to occur, would be dangerous, should be monitored carefully if ARTHROTEC is prescribed. The incidence of diarrhea can be minimized by administering ARTHROTEC with food and by avoiding coadministration with magnesium-containing antacids.

Gynecological

Gynecological disorders previously reported with misoprostol use have also been reported for women receiving ARTHROTEC (see below). Postmenopausal vaginal bleeding may be related to administration of ARTHROTEC. If it occurs, diagnostic workup should be undertaken to rule out gynecological pathology [see Boxed Warnings, Contraindications (4) and Warnings and Precautions (5)].

Other adverse experiences reported occasionally with ARTHROTEC, diclofenac or other NSAIDs, or misoprostol are:

Body as a whole: asthenia, fatigue, malaise.

Central and peripheral nervous system: dizziness, drowsiness, headache, insomnia, paresthesia, vertigo.

Digestive: anorexia, appetite changes, constipation, dry mouth, dysphagia, esophageal ulceration, esophagitis, eructation, gastritis, gastroesophageal reflux, GI neoplasm benign, peptic ulcer, tenesmus, vomiting.

Female reproductive disorders: breast pain, dysmenorrhea, menstrual disorder, menorrhagia, vaginal hemorrhage.

Hemic and lymphatic system: epistaxis, leukopenia, melena, purpura, decreased hematocrit.

Metabolic and nutritional: alanine aminotransferase increased, alkaline phosphatase increased, aspartate aminotransferase increased, dehydration, hyponatremia.

Musculoskeletal system: arthralgia, myalgia.

Psychiatric: anxiety, concentration impaired, depression, irritability.

Respiratory system: asthma, coughing, hyperventilation.

Skin and appendages: alopecia, eczema, pemphigoid reaction, photosensitivity, sweating increased, pruritus.

Special senses: taste perversion, tinnitus.

Renal and urinary disorders: dysuria, nocturia, polyuria, proteinuria, urinary tract infection.

Vision: diplopia.

6.2 Postmarketing Experience

The following adverse reactions have been identified during post approval of ARTHROTEC, diclofenac or misoprostol. Because these reactions are reported voluntarily from a population of uncertain size, it is not always possible to reliable estimate their frequency or establish a causal relationship to drug exposure.

Body as a whole: death, fever, infection, sepsis, chills, edema.

Cardiovascular system: arrhythmia, atrial fibrillation, congestive heart failure, hypertension, hypotension, increased creatine phosphokinase (CPK), increased lactate dehydrogenase (LDH), myocardial infarction, palpitations, phlebitis, premature ventricular contractions, syncope, tachycardia, vasculitis.

Central and peripheral nervous system: coma, convulsions, hyperesthesia, hypertonia, hypoesthesia, meningitis, migraine, neuralgia, somnolence, stroke, tremor.

Congenital, familial and genetic disorders: birth defects.

Digestive: enteritis, GI bleeding, glossitis, heartburn, hematemesis, hemorrhoids, intestinal perforation, stomatitis and ulcerative stomatitis.

Female reproductive disorders: intermenstrual bleeding, leukorrhea, vaginitis, uterine cramping, uterine hemorrhage.

Hemic and lymphatic system: agranulocytosis, anemia, aplastic anemia, coagulation time increased, ecchymosis, eosinophilia, hemolytic anemia, leukocytosis, lymphadenopathy, pancytopenia, pulmonary embolism, rectal bleeding, thrombocythemia, thrombocytopenia.

Hypersensitivity: angioedema, laryngeal/pharyngeal edema, urticaria.

Liver and biliary system: abnormal hepatic function, bilirubinemia, liver failure, pancreatitis, hepatitis, jaundice.

Male reproductive disorders: impotence, perineal pain.

Metabolic and nutritional: blood urea nitrogen (BUN) increased, glycosuria, gout, hypercholesterolemia, hyperglycemia, hyperuricemia, hypoglycemia, periorbital edema, porphyria, weight changes, fluid retention.

Pregnancy, puerperium and perinatal conditions: abnormal uterine contractions, uterine rupture/perforation, retained placenta, amniotic fluid embolism, incomplete abortion, premature birth, fetal death.

Psychiatric: confusion, disorientation, dream abnormalities, hallucinations, nervousness, paranoia, psychotic reaction.

Reproductive system and breast disorders: female fertility decreased.

Respiratory system: dyspnea, pneumonia, respiratory depression.

Skin and appendages: acne, bruising, erythema multiforme, exfoliative dermatitis, pruritus ani, rash, skin ulceration, Stevens-Johnson Syndrome (SJS), toxic epidermal necrolysis (TEN), fixed drug eruption (FDE), cutaneous reactions (bullous eruption).

Special senses: hearing impairment, taste loss.

Renal and urinary disorders: cystitis, hematuria, interstitial nephritis, micturition frequency, nephrotic syndrome, oliguria, papillary necrosis, renal failure, glomerulonephritis membranous, glomerulonephritis minimal lesion, glomerulonephritis.

Vision: amblyopia, blurred vision, conjunctivitis, glaucoma, iritis, lacrimation abnormal, night blindness, vision abnormal.

7 DRUG INTERACTIONS

See Table 1 for clinically significant drug interactions with diclofenac and misoprostol.

Table 1: Clinically Significant Drug Interactions with Diclofenac and Misoprostol
Drugs That Interfere with Hemostasis
Clinical Impact: | - Diclofenac and anticoagulants such as warfarin have a synergistic effect on bleeding. The concomitant use of diclofenac and anticoagulants have an increased risk of serious bleeding compared to the use of either drug alone. - Serotonin release by platelets plays an important role in hemostasis. Case-control and cohort epidemiological studies showed that concomitant use of drugs that interfere with serotonin reuptake and an NSAID may potentiate the risk of bleeding more than an NSAID alone.
Intervention: | Monitor patients with concomitant use of ARTHROTEC with anticoagulants (e.g., warfarin), antiplatelet drugs (e.g., aspirin), SSRIs, and SNRIs for signs of bleeding [see Warnings and Precautions (5.12)].
Aspirin
Clinical Impact: | Controlled clinical studies showed that the concomitant use of NSAIDs and analgesic doses of aspirin does not produce any greater therapeutic effect than the use of NSAIDs alone. In a clinical study, the concomitant use of an NSAID and aspirin was associated with a significantly increased incidence of GI adverse reactions as compared to use of the NSAID alone [see Warnings and Precautions (5.3)].
Intervention: | Concomitant use of ARTHROTEC and analgesic doses of aspirin is not generally recommended because of the increased risk of bleeding [see Warnings and Precautions (5.12)]. ARTHROTEC is not a substitute for low dose aspirin for cardiovascular protection.
ACE Inhibitors, Angiotensin Receptor Blockers, and Beta-Blockers
Clinical Impact: | - NSAIDs may diminish the antihypertensive effect of ACE inhibitors, ARBs, or beta-blockers (including propranolol). - In patients who are elderly, volume-depleted (including those on diuretic therapy), or have renal impairment, co-administration of an NSAID with ACE inhibitors or ARBs may result in deterioration of renal function, including possible acute renal failure. These effects are usually reversible.
Intervention: | - The concomitant administration of these drugs should be done with caution. Patients should be adequately hydrated and the clinical need to monitor the renal function should be assessed at the beginning of the concomitant treatment and periodically thereafter. - During concomitant use of ARTHROTEC and ACE inhibitors, ARBs, or beta-blockers, monitor blood pressure to ensure that the desired blood pressure is obtained. - During concomitant use of ARTHROTEC and ACE inhibitors or ARBs in patients who are elderly, volume-depleted, or have impaired renal function, monitor for signs of worsening renal function [see Warnings and Precautions (5.7)].
Diuretics
Clinical Impact: | Clinical studies, as well as post-marketing observations, showed that NSAIDs reduced the natriuretic effect of loop diuretics (e.g., furosemide) and thiazide diuretics in some patients. This effect has been attributed to the NSAID inhibition of renal prostaglandin synthesis.
Intervention: | During concomitant use of ARTHROTEC with diuretics, observe patients for signs of worsening renal function, in addition to assuring diuretic efficacy including antihypertensive effects [see Warnings and Precautions (5.7)].
Digoxin
Clinical Impact: | The concomitant use of diclofenac with digoxin has been reported to increase the serum concentration and prolong the half-life of digoxin.
Intervention: | During concomitant use of ARTHROTEC and digoxin, monitor serum digoxin levels.
Lithium
Clinical Impact: | NSAIDs have produced elevations in plasma lithium levels and reductions in renal lithium clearance. The mean minimum lithium concentration increased 15%, and the renal clearance decreased by approximately 20%. This effect has been attributed to NSAID inhibition of renal prostaglandin synthesis.
Intervention: | During concomitant use of ARTHROTEC and lithium, monitor patients for signs of lithium toxicity.
Methotrexate
Clinical Impact: | Concomitant use of NSAIDs and methotrexate may increase the risk for methotrexate toxicity (e.g., neutropenia, thrombocytopenia, renal dysfunction).
Intervention: | During concomitant use of ARTHROTEC and methotrexate, monitor patients for methotrexate toxicity.
Cyclosporine
Clinical Impact: | Concomitant use of diclofenac and cyclosporine may increase cyclosporine's nephrotoxicity.
Intervention: | During concomitant use of ARTHROTEC and cyclosporine, monitor patients for signs of worsening renal function.
NSAIDs and Salicylates
Clinical Impact: | Concomitant use of diclofenac with other NSAIDs or salicylates (e.g., diflunisal, salsalate) increases the risk of GI toxicity, with little or no increase in efficacy [see Warnings and Precautions (5.3)].
Intervention: | The concomitant use of ARTHROTEC with other NSAIDs or salicylates is not recommended.
Pemetrexed
Clinical Impact: | Concomitant use of diclofenac and pemetrexed may increase the risk of pemetrexed-associated myelosuppression, renal, and GI toxicity (see the pemetrexed prescribing information).
Intervention: | During concomitant use of ARTHROTEC and pemetrexed, in patients with renal impairment whose creatinine clearance ranges from 45 to 79 mL/min, monitor for myelosuppression, renal and GI toxicity. Avoid ARTHROTEC for a period of two days before, the day of, and two days following administration of pemetrexed.
Antacids
Clinical Impact: | Antacids reduce the bioavailability of misoprostol acid. Antacids may also delay absorption of diclofenac. Magnesium-containing antacids exacerbate misoprostol-associated diarrhea.
Intervention: | Concomitant use of ARTHROTEC and magnesium-containing antacids is not recommended.
Corticosteroids
Clinical Impact: | Concomitant use of corticosteroids with diclofenac may increase the risk of GI ulceration or bleeding.
Intervention | Monitor patients with concomitant use of ARTHROTEC with corticosteroids for signs of bleeding [see Warnings and Precautions (5.3)].
CYP2C9 Inhibitors or Inducers
Clinical Impact: | Diclofenac is metabolized by cytochrome P450 enzymes, predominantly by CYP2C9. Co-administration of diclofenac with CYP2C9 inhibitors (e.g., voriconzaole) may enhance the exposure and toxicity of diclofenac [see Clinical Pharmacology (12.3)] whereas co-administration with CYP2C9 inducers (e.g., rifampin) may lead to compromised efficacy of diclofenac.
Intervention: | CYP2C9 inhibitors: When concomitant use of CYP2C9 inhibitors is necessary, the total daily dose of diclofenac should not exceed the lowest recommended dose of ARTHROTEC 50 twice daily [see Dosage and Administration (2.4)]. CYP2C9 inducers: A dosage adjustment may be warranted when ARTHROTEC is administered with CYP2C9 inducers. Administer the separate products of misoprostol and diclofenac if a higher dose of diclofenac is deemed necessary.

8 USE IN SPECIFIC POPULATIONS

8.1 Pregnancy

Risk Summary

ARTHROTEC is contraindicated in pregnant women [see Contraindications (4)]. If a woman becomes pregnant while taking ARTHROTEC, discontinue the drug and advise the woman of the potential risks to her and to a fetus.

There are no adequate and well-controlled studies of ARTHROTEC in pregnant women; however, there is information available about the active drug components of ARTHROTEC, diclofenac sodium and misoprostol. Administration of misoprostol to pregnant women can cause uterine rupture, abortion, premature birth, or birth defects [see Warnings and Precautions (5.1)]. Congenital anomalies sometimes associated with fetal death have been reported subsequent to the unsuccessful use of misoprostol as an abortifacient, but the drug's teratogenic mechanism has not been demonstrated. Use of NSAIDS, including diclofenac a component of ARTHROTEC, can cause premature closure of the fetal ductus arteriosus and fetal renal dysfunction leading to oligohydramnios and, in some cases, neonatal renal impairment (see Data). There are clinical considerations when misoprostol and diclofenac are used in pregnant women (see Clinical Considerations). In reproduction studies with pregnant rabbits, there were no skeletal or visceral malformations when the combination of diclofenac sodium and misoprostol was administered during organogenesis at doses less than the maximum recommended human doses (MRHD); however, embryotoxicity was observed at this exposure (see Data). Based on animal data, prostaglandins have been shown to have an important role in endometrial vascular permeability, blastocyst implantation, and decidualization. In animal studies, administration of prostaglandin synthesis inhibitors such as diclofenac, resulted in increased pre- and post-implantation loss.

The estimated background risk of major birth defects and miscarriage for the indicated population is unknown. All pregnancies have a background risk of birth defect, loss, or other adverse outcomes. The estimated background risk of major birth defects and miscarriage in clinically recognized pregnancies is 2% to 4% and 15% to 20%, respectively.

Clinical Considerations

Maternal Adverse Reactions

Misoprostol may produce uterine contractions, uterine bleeding, and expulsion of the products of conception. Misoprostol has been used to ripen the cervix, to induce labor, and to treat postpartum hemorrhage, outside of its approved indication. A major adverse effect of these uses is hyperstimulation of the uterus. Uterine rupture, amniotic fluid embolism, severe bleeding, shock, and maternal death have been reported when misoprostol was administered to pregnant women to induce labor to induce abortion beyond the eighth week of pregnancy. Higher doses of misoprostol, including the 100 mcg tablet, may increase the risk of complications from uterine hyperstimulation. ARTHROTEC, which contains 200 mcg of misoprostol, is likely to have a greater risk of uterine hyperstimulation than the 100 mcg tablet of misoprostol. Abortions caused by misoprostol may be incomplete.

Cases of amniotic fluid embolism, which resulted in maternal and fetal death, have been reported with use of misoprostol during pregnancy. Severe vaginal bleeding, retained placenta, shock, and pelvic pain have also been reported. These women were administered misoprostol vaginally and/or orally over a range of doses.

ARTHROTEC is contraindicated in pregnant women [see Contraindications (4)].

If a woman is or becomes pregnant while taking this drug, the drug should be discontinued and the patient apprised of the potential hazard to the fetus.

Fetal/Neonatal Adverse Reactions

Misoprostol

Misoprostol may endanger pregnancy (may cause abortion) and thereby cause harm to the fetus when administered to a pregnant woman. Use of misoprostol for the induction of labor in the third trimester was associated with uterine hyperstimulation with resulting changes in the fetal heart rate (fetal bradycardia) and fetal death (misoprostol is not approved for this use). ARTHROTEC is contraindicated in pregnant women [see Contraindications (4)].

Diclofenac

Premature Closure of Fetal Ductus Arteriosus:

NSAIDs, including diclofenac, can cause premature closure of the fetal ductus arteriosus at about 30 weeks gestation and later in pregnancy (see Data).

Oligohydramnios/Neonatal Renal Impairment:

Use of NSAIDs, including diclofenac, at about 20 weeks gestation or later in pregnancy has been associated with cases of fetal renal dysfunction leading to oligohydramnios, and in some cases, neonatal renal impairment (see Data).

Labor or Delivery

There are no studies on the effects of ARTHROTEC or diclofenac during labor or delivery. In animal studies, NSAIDS, including diclofenac, inhibit prostaglandin synthesis, cause delayed parturition, and increase the incidence of stillbirth. In humans, some case reports and studies have associated misoprostol with risk of stillbirth, uterine hyperstimulation, perineal tear, amniotic fluid embolism, severe bleeding, shock, uterine rupture and death. The risk of uterine rupture associated with misoprostol use in pregnancy may occur at any gestational age, and increases with advancing gestational age and with prior uterine surgery, including cesarean delivery. Grand multiparity also appears to be a risk factor for uterine rupture.

Data

Human Data

Misoprostol

Several reports in the literature associate the use of misoprostol during the first trimester of pregnancy with skull defects, cranial nerve palsies, facial malformations, and limb defects.

Diclofenac

Data from observational studies regarding potential embryo-fetal risks of NSAID use (including diclofenac) in the first or second trimesters of pregnancy are inconclusive.

Premature Closure of Fetal Ductus Arteriosus:

Published literature reports that the use of NSAIDs at about 30 weeks of gestation and later in pregnancy may cause premature closure of the fetal ductus arteriosus.

Oligohydramnios/Neonatal Renal Impairment:

Published studies and postmarketing reports describe maternal NSAID use at about 20 weeks gestation or later in pregnancy associated with fetal renal dysfunction leading to oligohydramnios, and in some cases, neonatal renal impairment. These adverse outcomes are seen, on average, after days to weeks of treatment, although oligohydramnios has been infrequently reported as soon as 48 hours after NSAID initiation. In many cases, but not all, the decrease in amniotic fluid was transient and reversible with cessation of the drug. There have been a limited number of case reports of maternal NSAID use and neonatal renal dysfunction without oligohydramnios, some of which were irreversible. Some cases of neonatal renal dysfunction required treatment with invasive procedures, such as exchange transfusion or dialysis.

Methodological limitations of these postmarketing studies and reports include lack of a control group; limited information regarding dose, duration, and timing of drug exposure; and concomitant use of other medications. These limitations preclude establishing a reliable estimate of the risk of adverse fetal and neonatal outcomes with maternal NSAID use. Because the published safety data on neonatal outcomes involved mostly preterm infants, the generalizability of certain reported risks to the full-term infant exposed to NSAIDs through maternal use is uncertain.

Animal Data

The reproductive and developmental effects of both the combination of diclofenac sodium and misoprostol and each component of ARTHROTEC alone have been studied in animals. In all studies there was no evidence of teratogenicity. In an oral teratology study in pregnant rabbits, ARTHROTEC was administered at dose combinations (diclofenac and misoprostol, 250:1 ratio) up to 10 mg/kg/day diclofenac sodium (120 mg/m^2/day, 0.8 times the MRHD based on body surface area) and 0.04 mg/kg/day misoprostol (0.48 mg/m^2/day, 0.8 times the MRHD based on body surface area) and there was no evidence of teratogenicity. At the high dose, there was evidence of embryotoxicity (resorption and decreased fetal body weight) and maternal toxicity (decreased food intake and weight gain).

In oral teratology studies with misoprostol in pregnant rats at doses up to 1.6 mg/kg/day (9.6 mg/m^2/day, 16 times the MRHD based on body surface area) and pregnant rabbits at doses up to 1.0 mg/kg/day (12 mg/m^2/day, 20 times the MRHD based on body surface area), there was no evidence of teratogenicity.

In oral teratology studies with diclofenac sodium in pregnant mice at doses up to 20 mg/kg/day (60 mg/m^2/day, 0.4 times the MRHD based on body surface area), pregnant rats at doses up to 10 mg/kg/day (60 mg/m^2/day, 0.4 times the MRHD based on body surface area) and pregnant rabbits at doses up to 10 mg/kg/day (120 mg/m^2/day, 0.8 times the MRHD based on body surface area), there was no evidence of teratogenicity.

8.2 Lactation

Risk Summary

No lactation studies have been conducted with ARTHROTEC; however, limited published literature reports that diclofenac and the active metabolite of misoprostol are present in breast milk [see Clinical Pharmacology (12.3)]. The developmental and health benefits of breastfeeding should be considered along with the mother's clinical need for ARTHROTEC and any potential adverse effects on the breastfed infant from the ARTHROTEC or from the underlying maternal condition.

8.3 Females and Males of Reproductive Potential

ARTHROTEC is not recommended in women of childbearing potential [see Warnings and Precautions (5.1)]. If ARTHROTEC is prescribed, patients must be advised of the abortifacient property and warned not to give the drug to others.

Pregnancy Testing

Verify pregnancy status for females of reproductive potential within 2 weeks prior to initiating ARTHROTEC.

Contraception

Females

ARTHROTEC can cause fetal harm when administered to a pregnant woman [see Contraindications (4) and Use in Specific Populations (8.1)]. Advise females of reproductive potential to use effective contraception during treatment with ARTHROTEC.

ARTHROTEC may be prescribed if the patient:

- has had a negative serum pregnancy test within 2 weeks prior to beginning therapy.
- is capable of complying with effective contraceptive measures.
- has received both oral and written warnings of the hazards of misoprostol, the risk of possible contraception failure, and the danger to other women of childbearing potential should the drug be taken by mistake.
- will begin ARTHROTEC only on the second or third day of the next normal menstrual period.

Advise females to inform their healthcare provider of a known or suspected pregnancy.

Infertility

Females

Based on the mechanism of action, the use of prostaglandin-mediated NSAIDs, including diclofenac, a component of ARTHROTEC, may delay or prevent rupture of ovarian follicles, which has been associated with reversible infertility in some women [see Clinical Pharmacology (12.1)]. Published animal studies have shown that administration of prostaglandin synthesis inhibitors has the potential to disrupt prostaglandin-mediated follicular rupture required for ovulation. Small studies in women treated with NSAIDs have also shown a reversible delay in ovulation. Consider withdrawal of NSAIDs, including ARTHROTEC, in women who have difficulties conceiving or who are undergoing investigation of infertility.

8.4 Pediatric Use

Safety and effectiveness of ARTHROTEC in pediatric patients have not been established.

8.5 Geriatric Use

Geriatric patients (those 65 years of age and older), compared to younger adult patients, are at greater risk for NSAID-associated serious cardiovascular, gastrointestinal, and/or renal adverse reactions [see Warnings and Precautions (5.2, 5.3, 5.7)]. In addition, the risk of diclofenac-associated adverse reactions may be greater in geriatric patients with renal impairment or those taking concomitant ACE inhibitors or ARBs [see Drug Interactions (7) and Use in Specific Populations (8.6)].

Avoid use of ARTHROTEC in geriatric patients with cardiovascular and/or renal risk factors. If use cannot be avoided, use the lowest recommended dosage for the shortest duration and monitor for cardiac and renal adverse reactions [see Dosage and Administration (2.1)]. Monitor renal function in geriatric patients during treatment with ARTHROTEC, especially in patients with concomitant use of ACE inhibitors or ARBs.

Of the 2,184 patients in clinical studies with ARTHROTEC, 557 (25.5%) were 65 years of age and over. No overall differences in effectiveness were observed between these patients and younger adult patients, and other reported clinical experience has not identified differences in effectiveness between geriatric patients and younger adult patients, but greater sensitivity of some older individuals cannot be ruled out.

No clinically meaningful differences in the pharmacokinetics of diclofenac and misoprostol were observed in geriatric patients compared to younger adult patients [see Clinical Pharmacology (12.3)].

8.6 Renal Impairment

Diclofenac and misoprostol are primarily excreted by the kidney. Long-term administration of NSAIDs has resulted in renal toxicity. Correct volume status in dehydrated or hypovolemic patients prior to initiating ARTHROTEC. Monitor renal function, especially during concomitant use of ACE inhibitors or ARBs. Also, monitor renal function in patients with hepatic impairment. Avoid the use of ARTHROTEC in patients with advanced renal disease. If use cannot be avoided in patients with advanced renal disease, use the lowest dosage for the shortest duration, monitor the patient's renal function and monitor for clinical signs of worsening renal function [see Warnings and Precautions (5.7), Drug Interactions (7) and Clinical Pharmacology (12.3)].

10 OVERDOSAGE

Manage patients with symptomatic and supportive care following an acute NSAID overdosage. There are no specific antidotes. It is advisable to contact a poison control center (1-800-222-1222) to determine the latest recommendations because strategies for the management of overdose are continually evolving.

The toxic dose of ARTHROTEC has not been determined. However, signs of overdosage from the components of the product have been described.

Diclofenac

Symptoms following acute NSAID overdosages have been typically limited to lethargy, drowsiness, nausea, vomiting, and epigastric pain, which have been generally reversible with supportive care. Gastrointestinal bleeding has occurred. Hypertension, acute renal failure, respiratory depression, and coma have occurred, but were rare [see Warnings and Precautions (5.2, 5.3, 5.5, 5.7)].

Clinical signs that may suggest diclofenac sodium overdose include GI complaints, confusion, drowsiness, or general hypotonia.

If gastric decontamination may be potentially beneficial to the patient, e.g., short time since ingestion or a large overdosage (5 to 10 times the recommended dosage), consider emesis and/or activated charcoal (60 grams to 100 grams in adults, 1 gram to 2 grams per kg of body weight in pediatric patients) and/or an osmotic cathartic in symptomatic patients. Forced diuresis, alkalinization of urine, hemodialysis, or hemoperfusion may not be useful due to high protein binding.

Misoprostol

The toxic dose of misoprostol in humans has not been determined. Cumulative total daily doses of 1600 mcg have been tolerated, with only symptoms of GI discomfort being reported. Clinical signs that may indicate an overdose are sedation, tremor, convulsions, dyspnea, abdominal pain, diarrhea, fever, palpitations, hypotension, or bradycardia.

ARTHROTEC

Symptoms of acute overdosage with ARTHROTEC should be treated with supportive and symptomatic therapy. There are no specific antidotes. In case of acute overdosage, emesisis and/or gastric lavage may be considered dependent upon amount ingested and time since ingestion. The use of oral activated charcoal may help to reduce the absorption of diclofenac sodium and misoprostol. Induced diuresis may be beneficial because diclofenac sodium and misoprostol metabolites are excreted in the urine. The effect of dialysis or hemoperfusion on the elimination of diclofenac sodium (99% protein bound) and misoprostol acid remains unproven.

11 DESCRIPTION

ARTHROTEC is a combination product containing diclofenac sodium, an NSAID with analgesic properties, and misoprostol, a gastrointestinal (GI) mucosal protective prostaglandin-1 (PGE1) analog. ARTHROTEC tablets are white to off-white, round, biconvex, and approximately 11 mm in diameter. Each tablet consists of an enteric-coated core containing 50 mg (ARTHROTEC 50) or 75 mg (ARTHROTEC 75) of diclofenac sodium (equivalent to 46.39 mg or 69.58 mg of diclofenac, respectively) surrounded by an outer mantle containing 200 mcg misoprostol.

Diclofenac sodium is a phenylacetic acid derivative that is a white to off-white, virtually odorless, crystalline powder. Diclofenac sodium is freely soluble in methanol, soluble in ethanol, and practically insoluble in chloroform and in dilute acid. Diclofenac sodium is sparingly soluble in water. Its chemical formula and name are:

C14H10Cl2NO2Na [M.W. = 318.14] 2-[(2,6-dichlorophenyl) amino] benzeneacetic acid, monosodium salt.

Misoprostol is a water-soluble, viscous liquid that contains approximately equal amounts of two diastereomers. Its chemical formula and name are:

C22H38O5 [M.W. = 382.54] (±) methyl 11α,16-dihydroxy-16-methyl-9-oxoprost-13E-en-1-oate.

Inactive ingredients in ARTHROTEC include: colloidal silicon dioxide; crospovidone; hydrogenated castor oil; hypromellose; lactose; magnesium stearate; methacrylic acid copolymer; microcrystalline cellulose; povidone (polyvidone) K-30; sodium hydroxide; starch (corn); talc; triethyl citrate.

12 CLINICAL PHARMACOLOGY

12.1 Mechanism of Action

ARTHROTEC is a combination product containing diclofenac sodium, an NSAID with analgesic, anti-inflammatory and antipyretic properties, and misoprostol, a GI mucosal protective prostaglandin-1 (PGE1) analog.

Diclofenac

The mechanism of action of diclofenac, like that of other NSAIDs, is not completely understood but involves inhibition of cyclooxygenase (COX-1 and COX-2).

Diclofenac is a potent inhibitor of prostaglandin (PG) synthesis in vitro. Diclofenac concentrations reached during therapy have produced in vivo effects. Prostaglandins sensitize afferent nerves and potentiate the action of bradykinin in inducing pain in animal models. Prostaglandins are mediators of inflammation. Because diclofenac is an inhibitor of prostaglandin synthesis, its mode of action may be due to a decrease of prostaglandins in peripheral tissues.

Misoprostol

Misoprostol is a synthetic PGE1 analog with gastric antisecretory and mucosal protective properties. NSAIDs inhibit prostaglandin synthesis. A deficiency of prostaglandins within the gastric and duodenal mucosa may lead to diminishing bicarbonate and mucus secretion and may contribute to the mucosal damage caused by NSAIDs.

Misoprostol can increase bicarbonate and mucus production, but it has been shown at doses 200 mcg and above that are also antisecretory. It is therefore not possible to differentiate whether the ability of misoprostol to reduce the risk of gastric and duodenal ulcers is the result of its antisecretory effect, its mucosal protective effect, or both.

In vitro studies on canine parietal cells using titrated misoprostol acid as the ligand have led to the identification and characterization of specific prostaglandin receptors. Receptor binding is saturable, reversible, and stereo-specific. The sites have a high affinity for misoprostol, for its acid metabolite, and for other E type prostaglandins, but not for F or I prostaglandins and other unrelated compounds, such as histamine or cimetidine. Receptor-site affinity for misoprostol correlates well with an indirect index of antisecretory activity. It is likely that these specific receptors allow misoprostol taken with food to be effective topically, despite the lower serum concentrations attained.

Misoprostol, over the range of 50 mcg to 200 mcg, inhibits basal and nocturnal gastric acid secretion, and acid secretion in response to a variety of stimuli, including meals, histamine, pentagastrin, and coffee. Activity is apparent 30 minutes after oral administration and persists for at least 3 hours. In general, the effects of 50 mcg were modest and shorter-lived, and only the 200 mcg dose had substantial effects on nocturnal secretion or on histamine- and meal-stimulated secretion.

Misoprostol also produces a moderate decrease in pepsin concentration during basal conditions, but not during histamine stimulation. It has no significant effect on fasting or postprandial gastrin nor intrinsic factor output.

12.3 Pharmacokinetics

General Pharmacokinetic Characteristics

The pharmacokinetic profiles of diclofenac and misoprostol administered as the fixed combination (ARTHROTEC 50 or 75) are similar to the profiles when the two drugs are administered as separate tablets (see Table 2). No pharmacokinetic interaction between the two drugs has been observed following multiple dosing. The diclofenac total exposure [area under the curve (AUC)] is dose-proportional within the range of 25 mg to 150 mg. Approximately dose-proportional increase in misoprostol exposure was also observed within the range of 200 mcg to 400 mcg. Neither diclofenac nor misoprostol accumulated in plasma following repeated doses of ARTHROTEC given every 12 hours under fasted conditions.

Table 2: Pharmacokinetic Parameters of Diclofenac and Misoprostol Acid Following Single Oral Doses of ARTHROTEC or Separate Products in Healthy Subjects
MISOPROSTOL ACID Mean (SD)
Treatment (n=36) | Cmax (pg/mL) | Tmax (hr) | AUC(0–4h) (pg∙hr/mL)
ARTHROTEC 50 | 441 (137) | 0.30 (0.13) | 266 (95)
Misoprostol | 478 (201) | 0.30 (0.10) | 295 (143)
ARTHROTEC 75 | 304 (110) | 0.26 (0.09) | 177 (49)
Misoprostol | 290 (130) | 0.35 (0.12) | 176 (58)
DICLOFENAC Mean (SD)
Treatment (n=36) | Cmax (ng/mL) | Tmax (hr) | AUC(0–12h) (ng∙hr/mL)
ARTHROTEC 50 | 1207 (364) | 2.4 (1.0) | 1380 (272)
Diclofenac Sodium | 1298 (441) | 2.4 (1.0) | 1357 (290)
ARTHROTEC 75 | 2025 (2005) | 2.0 (1.4) | 2773 (1347)
Diclofenac Sodium | 2367 (1318) | 1.9 (0.7) | 2609 (1185)
SD: Standard deviation of the mean; AUC: Area under the curve; Cmax: Peak concentration; Tmax: Time to peak concentration

Absorption

Diclofenac: Diclofenac is completely absorbed from the GI tract after oral administration under fasted condition, and peak plasma levels are achieved in 2 hours (range 1–4 hours), and the area under the plasma concentration curve (AUC) is dose-proportional within the range of 25 mg to 150 mg. Peak plasma levels are less than dose-proportional and are approximately 1.5 and 2.0 mcg/mL for 50 mg and 75 mg doses, respectively. The diclofenac in ARTHROTEC is in a pharmaceutical formulation that resists dissolution in the low pH of gastric fluid but allows a rapid release of drug in the higher pH environment of the duodenum. Only 50% of the absorbed dose is systemically available due to first pass metabolism (i.e., oral bioavailability is 50%).

Misoprostol: Misoprostol is rapidly absorbed following oral administration of ARTHROTEC, and misoprostol acid (active metabolite) reaches a maximum plasma concentration in approximately 20 minutes. Maximum plasma concentrations of misoprostol acid are diminished when the dose is taken with food, and total availability of misoprostol acid is reduced by use of concomitant antacid. Clinical trials were conducted with concomitant antacid; this effect does not appear to be clinically important.

Food decreases the multiple-dose bioavailability profile of ARTHROTEC 50 and ARTHROTEC 75.

Distribution

Diclofenac: The volume of distribution of diclofenac is approximately 0.55 L/kg. More than 99% of diclofenac is bound to plasma albumin.

Misoprostol: The plasma protein binding of misoprostol acid is less than 90% and is concentration-independent in the therapeutic range.

After a single oral dose of misoprostol to nursing mothers, misoprostol acid was excreted in breast milk. The maximum concentration of misoprostol acid in expressed breast milk was achieved within 1 hour after dosing and was 7.6 pg/mL (CV 37%) and 20.9 pg/mL (CV 77%) after single 200 mcg and 600 mcg misoprostol administration, respectively. The misoprostol acid concentrations in breast milk declined to <1 pg/mL at 5 hours post-dose. These data may not reflect drug level in mature milk and in a daily dosing regimen for osteoarthritis or rheumatoid arthritis.

Elimination

Metabolism

Diclofenac: Metabolism is predominantly mediated via CYP2C9 in the liver. Five metabolites (4'hydroxy-, 5-hydroxy-, 3'-hydroxy-, 4',5-dihydroxy- and 3'-hydroxy-4'-methoxy diclofenac) have been identified. The major metabolite (4'-hydroxy-diclofenac) has very weak pharmacologic activity.

Both diclofenac and its oxidative metabolites undergo glucuronidation or sulfation followed by biliary excretion. Acylglucuronidation mediated by UGT2B7 and oxidation mediated by CYP2C8 may also play a role in diclofenac metabolism. CYP3A4 is responsible for the formation of minor metabolites, 5-hydroxy and 3'-hydroxy-diclofenac.

Misoprostol: Undergoes rapid and extensive metabolism to its biologically active metabolite, misoprostol acid.

Excretion

Diclofenac: Diclofenac is eliminated through metabolism and subsequent urinary and biliary excretion of the glucuronide and the sulfate conjugates of the metabolites. Approximately 65% of the dose is excreted in the urine and 35% in the bile. The elimination half-life of diclofenac is approximately 2 hours. The clearance of diclofenac is approximately 350 mL/min (equivalent to 21 L/h).

Conjugates of unchanged diclofenac account for 5% to 10% of the dose excreted in the urine and for less than 5% excreted in the bile. Little or no unchanged unconjugated drug is excreted. Conjugates of the principal metabolite account for 20% to 30% of the dose excreted in the urine and for 10% to 20% of the dose excreted in the bile.

Conjugates of three other metabolites together account for 10% to 20% of the dose excreted in the urine and for small amounts excreted in the bile. The elimination half-life values for these metabolites are shorter than those for the parent drug. Urinary excretion of an additional metabolite (half-life = 80 hours) accounts for only 1.4% of the oral dose. The degree of accumulation of diclofenac metabolites is unknown. Some of the metabolites may have activity.

Misoprostol: After oral administration of radio-labeled misoprostol, approximately 70% of detected radioactivity appears in the urine. The elimination half-life is approximately 30 minutes.

Specific Populations

Geriatric Patients

No differences in the pharmacokinetics of diclofenac were observed in geriatric subjects (66 to 81 years; N=10) compared to younger adult subjects (26 to 46 years; N=10) following administration of diclofenac 50 mg twice daily for 4 weeks.

Though the mean AUC value of misoprostol acid for elderly subjects was 41% higher in geriatric healthy subjects (mean age, 69.5±4.6 years, N=24) compared to younger adult healthy subjects (mean age, 25.4±4.2 years, N=24) following single dose of misoprostol 400 µg, the increase in exposure is not clinically meaningful.

In a multiple-dose crossover study of ARTHROTEC administered twice daily to 24 subjects aged 65 years of age and older, misoprostol did not affect the pharmacokinetics of diclofenac [see Use in Specific Populations (8.5)].

Racial or Ethnic Groups

Pharmacokinetic differences due to race have not been identified.

Patients with Renal Impairment

In patients with renal impairment (N=5, creatinine clearance 3 to 42 mL/min) following intravenous administration of 50 mg diclofenac, AUC values and elimination rates were comparable to those in healthy subjects.

Pharmacokinetic studies with misoprostol in patients with severe renal impairment requiring hemodialysis (n=8, mean creatinine clearance 6.2±3.3 mL/min/1.73m^2) who received a single dose of 400 mcg misoprostol during a interdialytic period showed an approximate doubling of elimination half-life, Cmax, and AUC of misoprostol acid compared to healthy subjects [see Use in Specific Populations (8.6)].

Patients with Hepatic Impairment

In patients with biopsy-confirmed cirrhosis or chronic active hepatitis (variably elevated transaminases and mildly elevated bilirubin, N=10), diclofenac concentrations and urinary elimination values following administration of 100 mg oral solution were comparable to those in healthy subjects.

In a study of subjects with mild to moderate hepatic impairment, mean misoprostol acid AUC and Cmax showed approximately twice high as the mean values obtained in healthy subjects. Three subjects who had the lowest antipyrine and lowest indocyanine green clearance values had the highest misoprostol acid AUC and Cmax values.

Drug Interaction Studies

Diclofenac

Aspirin: When ARTHROTEC was administered with aspirin, the protein binding of diclofenac was reduced, although the clearance of the free diclofenac was not altered. The clinical significance of this interaction is not known. See Table 1 for clinically significant drug interactions of NSAIDs with aspirin [see Drug Interactions (7)].

Voriconazole: When a single dose diclofenac (50 mg) was coadministered with the last dose of voriconazole (400 mg every 12 hours on Day 1, followed by 200 mg every 12 hours on Day 2), the mean Cmax and AUC of diclofenac were increased by 114% and 78%, respectively, when compared to diclofenac alone [see Drug Interactions (7)].

In vitro, diclofenac interferes minimally with the protein binding of prednisolone (10% decrease in binding). Benzylpenicillin, ampicillin, oxacillin, chlortetracycline, doxycycline, cephalothin, erythromycin, and sulfamethoxazole have no influence, in vitro, on the protein binding of diclofenac in human serum.

Other drugs: In small groups of patients (7 to 10 patients/interaction study), the concomitant administration of azathioprine, gold, chloroquine, D-penicillamine, prednisolone, doxycycline or digitoxin did not significantly affect Cmax and AUC of diclofenac.

Misoprostol

Diazepam: Misoprostol given for 1 week had no effect on the steady state pharmacokinetics of diazepam when the two drugs were administered 2 hours apart.

Other drugs: Pharmacokinetic studies also showed a lack of drug interaction with antipyrine or propranolol given with misoprostol.

13 NONCLINICAL TOXICOLOGY

13.1 Carcinogenesis, Mutagenesis, Impairment of Fertility

Carcinogenesis

Long-term animal studies to evaluate the potential for carcinogenesis and animal studies to evaluate the effects on fertility have been performed with each component of ARTHROTEC given alone.

In a 24 month rat carcinogenicity study, misoprostol administered orally at doses up to 2.4 mg/kg/day (14.4 mg/m^2/day, 24 times the MRHD of 0.6 mg/m^2/day) was not tumorigenic. In a 21-month mouse carcinogenicity study, misoprostol administered orally at doses up to 16 mg/kg/day (48 mg/m^2/day), 80 times the MRHD based on body surface area, was not tumorigenic.

In a 24-month rat carcinogenicity study, diclofenac sodium administered orally at up to 2 mg/kg/day (12 mg/m^2/day) was not tumorigenic. In a 24-month mouse carcinogenicity study, oral diclofenac sodium at doses up to 0.3 mg/kg/day (0.9 mg/m^2/day, 0.006 times the MRHD based on body surface area) in males and 1 mg/kg/day (3 mg/m^2/day, 0.02 times the MRHD based on body surface area) in females was not tumorigenic.

Mutagenesis

Diclofenac sodium and misoprostol combination in 250:1 ratio was not genotoxic in the Ames test, the Chinese hamster ovary cell (CHO/HGPRT) forward mutation test, the rat lymphocyte chromosome aberration test, or the mouse bone marrow micronucleus test.

Impairment of Fertility

The effects of diclofenac sodium and misoprostol on male or female fertility have not been studied in animals; however, there are data with diclofenac sodium and misoprostol given alone. Misoprostol, when administered to male and female breeding rats in an oral dose range of 0.1 to 10 mg/kg/day (0.6 to 60 mg/m^2/day, 1 to 100 times the MRHD based on body surface area) produced dose-related pre- and post-implantation losses and a significant decrease in the number of live pups born at the highest dose (60 mg/m^2/day, 100 times the MRHD based on body surface area). Diclofenac sodium at oral doses up to 4 mg/kg/day (24 mg/m^2/day, 0.16 times the MRHD based on body surface area) was found to have no effect on fertility and reproductive performance of male and female rats.

13.2 Animal Toxicology

A reversible increase in the number of normal surface gastric epithelial cells occurred in the dog, rat, and mouse during long-term toxicology studies with misoprostol. No such increase has been observed in humans administered misoprostol for up to 1 year. An apparent response of the female mouse to misoprostol in long-term studies at 100 to 1000 times the human dose was hyperostosis, mainly of the medulla of sternebrae. Hyperostosis did not occur in long-term studies in the dog and rat and has not been seen in humans treated with misoprostol.

14 CLINICAL STUDIES

Osteoarthritis

Diclofenac sodium, as a single ingredient or in combination with misoprostol, has been shown to be effective in the management of the signs and symptoms of osteoarthritis.

Rheumatoid Arthritis

Diclofenac sodium, as a single ingredient or in combination with misoprostol, has been shown to be effective in the management of the signs and symptoms of rheumatoid arthritis.

Upper Gastrointestinal Safety

Diclofenac, and other NSAIDs, have caused serious gastrointestinal toxicity, such as bleeding, ulceration, and perforation of the stomach, small intestine or large intestine. Misoprostol has been shown to reduce the incidence of endoscopically diagnosed NSAID-induced gastric and duodenal ulcers. In a 12-week, randomized, double-blind, dose-response study, misoprostol 200 mcg administered four, three or two times a day, was significantly more effective than placebo in reducing the incidence of gastric ulcer in osteoarthritis and rheumatoid arthritis patients using a variety of NSAIDs. The three times a day regimen was therapeutically equivalent to misoprostol 200 mcg four times a day with respect to the prevention of gastric ulcers. Misoprostol 200 mcg given two times a day was less effective than 200 mcg given three or four times a day. The incidence of NSAID-induced duodenal ulcer was also significantly reduced with all three regimens of misoprostol compared to placebo (see Table 3).

Table 3
Misoprostol 200 mcg Dosage Regimen
 | Placebo | two times a day | three times a day | four times a day
Gastric ulcer | 11% | 6% [Misoprostol significantly different from placebo (p<0.05)] | 3% | 3%
Duodenal ulcer | 6% | 2% | 3% | 1%
N=1623; 12 weeks

Results of a study in 572 patients with osteoarthritis demonstrate that patients receiving ARTHROTEC have a lower incidence of endoscopically defined gastric ulcers compared to patients receiving diclofenac sodium (see Table 4).

Table 4
Osteoarthritis patients with history of ulcer or erosive disease (N=572), 6 weeks | Incidence of ulcers
Osteoarthritis patients with history of ulcer or erosive disease (N=572), 6 weeks | Gastric | Duodenal
ARTHROTEC 50 three times a day | 3% [Statistically significantly different from diclofenac (p<0.05)] | 6%
ARTHROTEC 75 two times a day | 4% | 3%
Diclofenac sodium 75 mg two times a day | 11% | 7%
Placebo | 3% | 1%

16 HOW SUPPLIED/STORAGE AND HANDLING

ARTHROTEC (diclofenac sodium and misoprostol delayed-release tablets) are supplied as:

- 50 mg diclofenac sodium and 200 mcg misoprostol as round, biconvex, white to off-white tablets imprinted with four "A's" encircling a "50" in the middle on one side and "SEARLE" and "1411" on the other.
- 75 mg diclofenac sodium and 200 mcg misoprostol as round, biconvex, white to off-white tablets imprinted with four "A's" encircling a "75" in the middle on one side and "SEARLE" and "1421" on the other.

The dosage strengths are supplied in:

Strength |  | NDC Number | Size
ARTHROTEC 50 | 50 mg diclofenac sodium and 200 mcg misoprostol | 0025-1411-60 | bottle of 60
ARTHROTEC 50 | 50 mg diclofenac sodium and 200 mcg misoprostol | 0025-1411-90 | bottle of 90
ARTHROTEC 75 | 75 mg diclofenac sodium and 200 mcg misoprostol | 0025-1421-60 | bottle of 60

STORAGE AND HANDLING

Store at 20°C to 25°C (68°F to 77°F). Excursions permitted to 15°C to 30°C (59°F to 86°F) [See USP Controlled Room Temperature].

17 PATIENT COUNSELING INFORMATION

Advise the patient to read the FDA-approved patient labeling (Medication Guide). Inform patients, families, or their caregivers of the following information before initiating therapy with ARTHROTEC and periodically during the course of ongoing therapy.

Uterine Rupture, Abortion, Premature Birth, or Birth Defects with Misoprostol and Embryo-Fetal Toxicity with NSAIDs

- Advise females that ARTHROTEC is contraindicated in pregnant women. Use of misoprostol, a component of ARTHROTEC during pregnancy can result in maternal and fetal harm, including uterine rupture, abortion, premature birth, or birth defects. Use of diclofenac may cause oligohydramnios/fetal renal dysfunction and premature closure of the fetal ductus arteriosus.
- Advise patients not to give ARTHROTEC to others.
- Advise females of reproductive potential of the potential risk to a fetus and to use effective contraception during treatment with ARTHROTEC. Advise females to inform their healthcare provider of a known or suspected pregnancy [see Contraindications (4), Warnings and Precautions (5.1), and Use in Specific Populations (8.1, 8.3)].

Infertility

Advise females of reproductive potential that ARTHROTEC may delay or prevent rupture of ovarian follicles, which has been associated with reversible infertility in some women [see Use in Specific Populations (8.3)].

Cardiovascular Thrombotic Events

Advise patients to be alert for the symptoms of cardiovascular thrombotic events, including chest pain, shortness of breath, weakness, or slurring of speech, and to report any of these symptoms to their health care provider immediately [see Warnings and Precautions (5.2)].

Gastrointestinal Bleeding, Ulceration, and Perforation

Advise patients to report symptoms of ulcerations and bleeding, including epigastric pain, dyspepsia, melena, and hematemesis to their health care provider. In the setting of concomitant use of low-dose aspirin for cardiac prophylaxis, inform patients of the increased risk for and the signs and symptoms of GI bleeding [see Warnings and Precautions (5.3)].

Hepatotoxicity

Inform patients of the warning signs and symptoms of hepatotoxicity (e.g., nausea, fatigue, lethargy, pruritus, diarrhea, jaundice, right upper quadrant tenderness, and "flu-like" symptoms). If these occur, instruct patients to stop ARTHROTEC and seek immediate medical therapy [see Warnings and Precautions (5.4)].

Heart Failure and Edema

Advise patients to be alert for the symptoms of congestive heart failure including shortness of breath, unexplained weight gain, or edema and to contact their healthcare provider if such symptoms occur [see Warnings and Precautions (5.6)].

Anaphylactic Reactions

Inform patients of the signs of an anaphylactic reaction (e.g., difficulty breathing, swelling of the face or throat). Instruct patients to seek immediate emergency help if these occur [see Contraindications (4) and Warnings and Precautions (5.8)].

Serious Skin Reactions, including DRESS

Advise patients to stop taking ARTHROTEC immediately if they develop any type of rash or fever and contact their healthcare provider as soon as possible [see Warnings and Precautions (5.10, 5.11)].

Avoid Concomitant Use of NSAIDs

Inform patients that the concomitant use of ARTHROTEC with other NSAIDs or salicylates (e.g., diflunisal, salsalate) is not recommended due to the increased risk of gastrointestinal toxicity, and little or no increase in efficacy [see Warnings and Precautions (5.3) and Drug Interactions (7)]. Alert patients that NSAIDs may be present in "over the counter" medications for treatment of colds, fever, or insomnia.

Use of NSAIDS and Low-Dose Aspirin

Inform patients not to use low-dose aspirin concomitantly with ARTHROTEC until they talk to their healthcare provider [see Drug Interactions (7)].

This product's labeling may have been updated. For the most recent prescribing information, please visit www.pfizer.com.

For medical information about Arthrotec, please visit www.pfizermedinfo.com or call 1‑800‑438-1985.

LAB-0061-32.0

MEDICATION GUIDE
Medication Guide for
ARTHROTEC (ARTH' roe-tek)
(diclofenac sodium and misoprostol delayed- release tablets) for oral use

What is the most important information I should know about ARTHROTEC?
ARTHROTEC contains diclofenac (a nonsteroidal anti-inflammatory drug (NSAID)) and misoprostol, and can cause uterus to tear (uterine rupture), abortion, premature birth, or birth defects. The risk of uterine rupture increases as your pregnancy advances, if you have given birth to 5 or more children, and if you have had surgery on the uterus, such as a cesarean delivery.
Do not take ARTHROTEC if you are pregnant.

- Tell your healthcare provider if you become pregnant or think you may be pregnant during treatment with ARTHROTEC. If you are able to become pregnant, your healthcare provider should do a pregnancy test before you start treatment with ARTHROTEC. Females who are able to become pregnant should use an effective form of birth control (contraception) during treatment with ARTHROTEC.

What is the most important information I should know about medicines containing Nonsteroidal Anti-inflammatory Drugs (NSAIDs)?
NSAIDs can cause serious side effects, including:

- Increased risk of a heart attack or stroke that can lead to death. This risk may happen early in treatment and may increase:
  - with increasing doses of NSAIDs
  - with longer use of NSAIDs

Do not take NSAID containing medicines right before or after a heart surgery called a "coronary artery bypass graft (CABG)."
Avoid taking NSAID containing medicines after a recent heart attack, unless your healthcare provider tells you to. You may have an increased risk of another heart attack if you take NSAIDs after a recent heart attack.

- Increased risk of bleeding, ulcers, and tears (perforation) of the esophagus (tube leading from the mouth to the stomach), stomach and intestines:
  - anytime during use
  - without warning symptoms
  - that may cause death

The risk of getting an ulcer or bleeding increases with:

- past history of stomach ulcers, or stomach or intestinal bleeding with use of NSAIDs
- taking medicines called "corticosteroids", "antiplatelet drugs", "anticoagulants", "SSRIs", or "SNRIs"

- increasing doses of NSAIDs
- longer use of NSAIDs
- smoking
- drinking alcohol

- older age
- poor health
- advanced liver disease
- bleeding problems

NSAID containing medicines should only be used:

- exactly as prescribed
- at the lowest dose possible for your treatment
- for the shortest time needed

What is ARTHROTEC?
ARTHROTEC contains 2 medicines:

1. Diclofenac is a non-steroidal anti-inflammatory drug (NSAID). See "What is the most important information I should know about medicines called Nonsteroidal Anti-inflammatory Drugs (NSAIDs)?
2. Misoprostol is a medicine used to protect the lining of the esophagus, stomach and intestines while taking diclofenac.

ARTHROTEC is a prescription medicine used to treat:

- symptoms of osteoarthritis or rheumatoid arthritis in adults at high risk of developing stomach (gastric) and intestinal (duodenal) ulcers while taking NSAIDs.

It is not known if ARTHROTEC is safe and effective for use in children.
What are NSAIDs?
NSAIDs are used to treat pain and redness, swelling, and heat (inflammation) from medical conditions such as different types of arthritis.

Who should not take ARTHROTEC?
Do not take ARTHROTEC:

- if you are pregnant.
- right before or after heart bypass surgery.
- if you currently have bleeding in your stomach (gastrointestinal bleeding).
- if you have had an asthma attack, hives, or other allergic reaction with aspirin or any other NSAIDs.
- if you are allergic to diclofenac sodium and misoprostol, other prostaglandins or any other ingredients in ARTHROTEC. See the end of this Medication Guide for a list of ingredients in ARTHROTEC.

Before taking ARTHROTEC, tell your healthcare provider about all of your medical conditions, including if you:

- have liver or kidney problems.
- have high blood pressure.
- have heart problems, including a history of heart failure or heart attack.
- have asthma.
- are pregnant or plan to become pregnant. See "Who should not take ARTHROTEC?"
- are breastfeeding or plan to breast feed.

Tell your healthcare provider about all of the medicines you take, including prescription and over-the-counter medicines, vitamins and herbal supplements. NSAIDs and some other medicines can interact with each other and cause serious side effects. Do not start taking any new medicine without talking to your healthcare provider first.

What are the possible side effects of NSAIDs?
NSAIDs can cause serious side effects, including:
See "What is the most important information I should know about medicines called Nonsteroidal Anti-inflammatory Drugs (NSAIDs)?

- new or worse high blood pressure
- heart failure
- liver problems including liver failure
- kidney problems including kidney failure
- low red blood cells (anemia)
- life-threatening skin reactions
- life-threatening allergic reactions
- asthma attacks in people who have asthma
- Other side effects of NSAIDs include: stomach pain, constipation, diarrhea, gas, heartburn, nausea, vomiting, and dizziness

Get emergency help right away if you get any of the following symptoms:

- shortness of breath or trouble breathing
- chest pain
- weakness in one part or side of your body

- slurred speech
- swelling of the face or throat

Stop taking your NSAID and call your healthcare provider right away if you get any of the following symptoms:

- nausea
- more tired or weaker than usual
- diarrhea
- itching
- your skin or eyes look yellow
- indigestion or stomach pain
- flu-like symptoms

- vomit blood
- there is blood in your bowel movement or it is black and sticky like tar
- unusual weight gain
- skin rash or blisters with fever
- swelling of the arms, legs, hands and feet

If you take too much of your NSAID, call your healthcare provider or get medical help right away.
These are not all the possible side effects of NSAIDs. For more information, ask your healthcare provider or pharmacist about NSAIDs.
Call your doctor for medical advice about side effects. You may report side effects to FDA at 1-800-FDA-1088.

Other information about NSAIDs

- Aspirin is an NSAID but it does not increase the chance of a heart attack. Aspirin can cause bleeding in the brain, stomach, and intestines. Aspirin can also cause ulcers in the stomach and intestines.
- Some NSAIDs are sold in lower doses without a prescription (over-the-counter). Talk to your healthcare provider before using over-the-counter NSAIDs for more than 10 days.

General information about the safe and effective use of NSAIDs
Medicines are sometimes prescribed for purposes other than those listed in a Medication Guide. Do not use NSAIDs for a condition for which it was not prescribed. Do not give NSAIDs to other people, even if they have the same symptoms that you have. It may harm them.
If you would like more information about NSAIDs, talk with your healthcare provider. You can ask your pharmacist or healthcare provider for information about NSAIDs that is written for health professionals.

Active ingredients: diclofenac sodium, misoprostol.
Inactive ingredients: colloidal silicon dioxide, crospovidone, hydrogenated castor oil, hypromellose, lactose, magnesium stearate, methacrylic acid copolymer, microcrystalline cellulose, povidone (polyvidone) K-30, sodium hydroxide, starch (corn), talc, triethyl citrate.
This product's labeling may have been updated. For the most recent prescribing information, please visit www.pfizer.com.
For more information, go to www.pfizer.com or call 1-800-438-1985.
LAB: 0793-9.0

This Medication Guide has been approved by the U.S. Food and Drug Administration.

Revised: November 2024

PRINCIPAL DISPLAY PANEL - 50 mg Tablet Label

Arthrotec® 50

50 mg diclofenac sodium/
200 mcg misoprostol

Distributed by
G.D. Searle LLC
Division of Pfizer Inc, NY, NY 10017

PRINCIPAL DISPLAY PANEL - 50 mg Tablet Bottle Label

ALWAYS DISPENSE WITH MEDICATION GUIDE

Pfizer

NDC 0025-1411-60

Arthrotec® 50
diclofenac sodium and misoprostol
delayed-release tablets

50 mg/200 mcg

DOSAGE AND USE
See accompanying prescribing information.

60 Tablets
Rx only

20689541

PRINCIPAL DISPLAY PANEL - 75 mg Tablet Label

Arthrotec® 75

75 mg diclofenac sodium/
200 mcg misoprostol

Distributed by
G.D. Searle LLC
Division of Pfizer Inc, NY, NY 10017

PRINCIPAL DISPLAY PANEL - 75 mg Tablet Bottle Label

ALWAYS DISPENSE WITH MEDICATION GUIDE

Pfizer

NDC 0025-1421-60

Arthrotec® 75
diclofenac sodium and misoprostol
delayed-release tablets

75 mg/200 mcg

DOSAGE AND USE
See accompanying prescribing information.

60 Tablets
Rx only

20689543